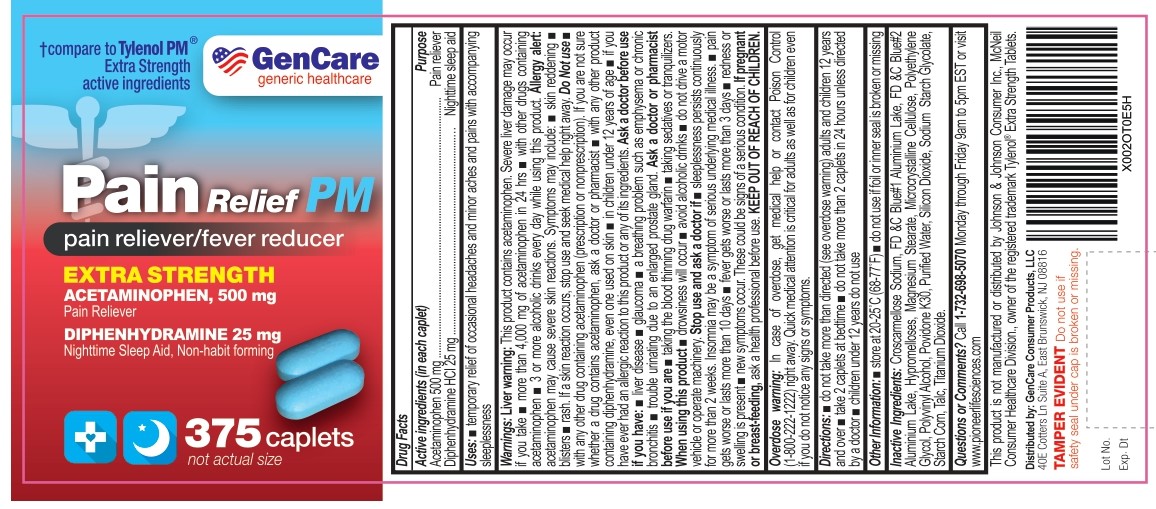 DRUG LABEL: Pain Relief PM
NDC: 72090-032 | Form: TABLET
Manufacturer: Pioneer Life Sciences, LLC
Category: otc | Type: HUMAN OTC DRUG LABEL
Date: 20251229

ACTIVE INGREDIENTS: DIPHENHYDRAMINE HYDROCHLORIDE 25 mg/1 1; ACETAMINOPHEN 500 mg/1 1
INACTIVE INGREDIENTS: CROSCARMELLOSE SODIUM; FD&C BLUE NO. 1 ALUMINUM LAKE; FD&C BLUE NO. 2 ALUMINUM LAKE; HYPROMELLOSE, UNSPECIFIED; MAGNESIUM STEARATE; MICROCRYSTALLINE CELLULOSE; POLYETHYLENE GLYCOL, UNSPECIFIED; POLYVINYL ALCOHOL; POVIDONE K30; SILICON DIOXIDE; SODIUM STARCH GLYCOLATE TYPE A; STARCH, CORN; TALC; TITANIUM DIOXIDE

Pain Relief PM

Active Ingredients (in each caplet)

Acetaminophen 500 mg

Diphenhydramine 25 mg

Purpose

Acetaminophen 500 mg ....................................................................................................................................Pain reliever
Diphenhydramine HCl 25 mg ...........................................................................….................................Nighttime sleep aid

Uses:

- temporary relief of occasional headaches and minor aches and pains with accompanying sleeplessness

Warnings:

Liver warning: This product contains acetaminophen. Severe liver damage may occur if you take ■ more than 4,000 mg of acetaminophen in 24 hrs ■ with other drugs containing acetaminophen ■ 3 or more alcoholic drinks every day while using this product.

Allergy alert: acetaminophen may cause severe skin reactions. Symptoms may include: ■ skin reddening ■ blisters ■ rash. If a skin reaction occurs, stop use and seek medical help right away.

Do Not use

■ with any other drug containing acetaminophen (prescription or nonprescription).
If you are not sure whether a drug contains acetaminophen, ask a doctor or pharmacist ■ with any other product containing diphenhydramine, even one used on skin ■ in children under 12 years of age ■ if you have ever had an allergic reaction to this product or any of its ingredients.

Ask a doctor before use if you have:

■ liver disease

■ glaucoma

■ a breathing problem such as emphysema or chronic bronchitis

■ trouble urinating due to an enlarged prostate gland.

Ask a doctor or pharmacist before use if you are

- taking the blood thinning drug warfarin
- taking sedatives or tranquilizers

When using this product

■ drowsiness will occur

■ avoid alcoholic drinks

■ do not drive a motor vehicle or operate machinery.

Stop use and ask a doctor if

■ sleeplessness persists continuously for more than 2 weeks. Insomnia may be a symptom of serious underlying medical illness.

■ pain gets worse or lasts more than 10 days

■ fever gets worse or lasts more than 3 days

■ redness or swelling is present

■ new symptoms occur. These could be signs of a serious condition.

If pregnant or breast-feeding

ask a health professional before use.

KEEP OUT OF REACH OF CHILDREN

Overdose warning: In case of overdose, get medical help or contact Poison Control (1-800-222-1222) right away.
Quick medical attention is critical for adults as well as for children even if you do not notice any signs or symptoms.

Directions:

■ do not take more than directed (see overdose warning) adults and children 12 years and over
■ take 2 caplets at bedtime

■ do not take more than 2 caplets in 24 hours unless directed by a doctor

■ children under 12 years do not use

Other Information:

- store at 20°-25°C (68°-77°F)
- do not use if foil or inner seal is broken or missing

Inactive Ingredients:

Croscarmellose Sodium, FD & C Blue#1 Aluminium Lake, FD &C Blue#2
Aluminium Lake, Hypromelloses, Magnesium Stearate, Microcrystalline Cellulose, Polyethylene
Glycol, Polyvinyl Alcohol, Povidone K30, Purified Water, Silicon Dioxide, Sodium Starch Glycolate,
Starch Corn, Talc, Titanium Dioxide.

Questions or Comments?

Call 1-732-698-5070 Monday through Friday 9am to 5pm EST or visit www.pioneerlifesciences.com

This product is not manufactured or distributed by Johnson & Johnson Consumer Inc., McNeil Consumer Healthcare
Division., owner of the registered trademark Tylenol® Extra Strength Tablets.

Distributed by: GenCare Consumer Products, LLC 40E Cotters Ln Suite A, East Brunswick, NJ 08816